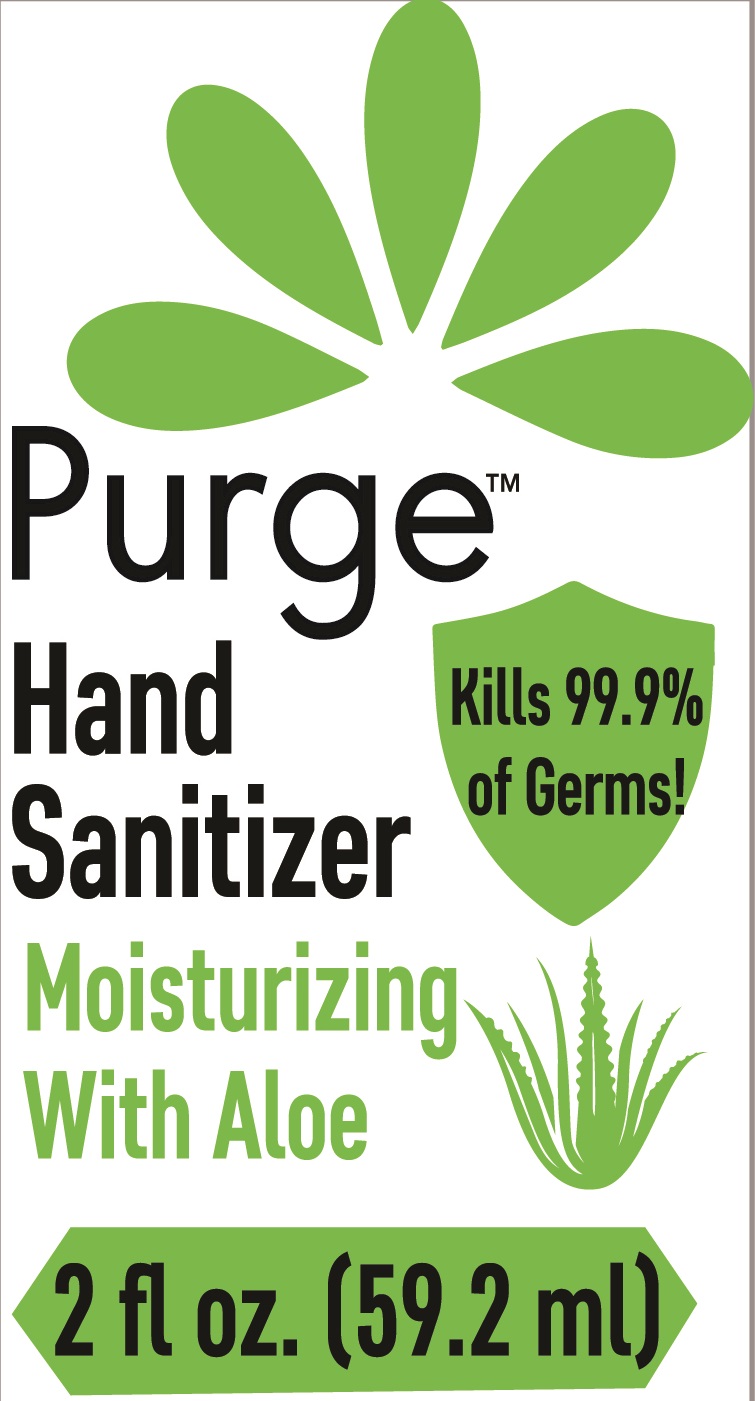 DRUG LABEL: Purge Hand Sanitizer
NDC: 78562-070 | Form: GEL
Manufacturer: Halpern Import Company
Category: otc | Type: HUMAN OTC DRUG LABEL
Date: 20200720

ACTIVE INGREDIENTS: ALCOHOL 70 mL/100 mL
INACTIVE INGREDIENTS: WATER; ALOE; POLYACRYLIC ACID (250000 MW); TROLAMINE

Purge

Active ingredient

Ethyl Alcohol 70%

Purpose

Antiseptic

Uses

- to decrease bacteria on the skin that could cause disease
- recommended for repeated use

Warnings

For external use only: hands
Flammable. Keep away from heat and flame

When using this product

- keep out of eyes. In case of contact with eyes, flush thoroughly with water
- avoid contact with broken skin
- do not inhale or ingest

Stop use and ask a doctor if

- irritation or redness develops
- condition persists for more than 72 hours

Keep out of reach of children.

If swallowed, get medical help or contact a Poison Control Center right away.

Directions

- wet hands thoroughly with product and allow to dry without wiping
- for children under 6, use only under adult supervision
- not recommended for infants

Other Information

- do not store above 105°F
- may discolor some fabrics
- harmful to wood finishes and plastics

*Effective at eliminating more than 99.9°/o of many common harmful germs and bacteria in as little as 15 seconds

Inactive ingredients

Water, Aloe, Polyacrylic Acid, Triethanolamine, Fragrance.

Principal Display Panel

NDC:78562-070-02, 78562-070-04, 78562-070-17 and 78562-070-34

PurgeTM

Hand Sanitizer

Moisturizing With Aloe

Kills 99.9% of Germs

2 fl oz. (59.2ml)

4 fl oz. (118.294 ml)

16.9 fl oz (500 ml)

33.8 fl oz (1000 ml)